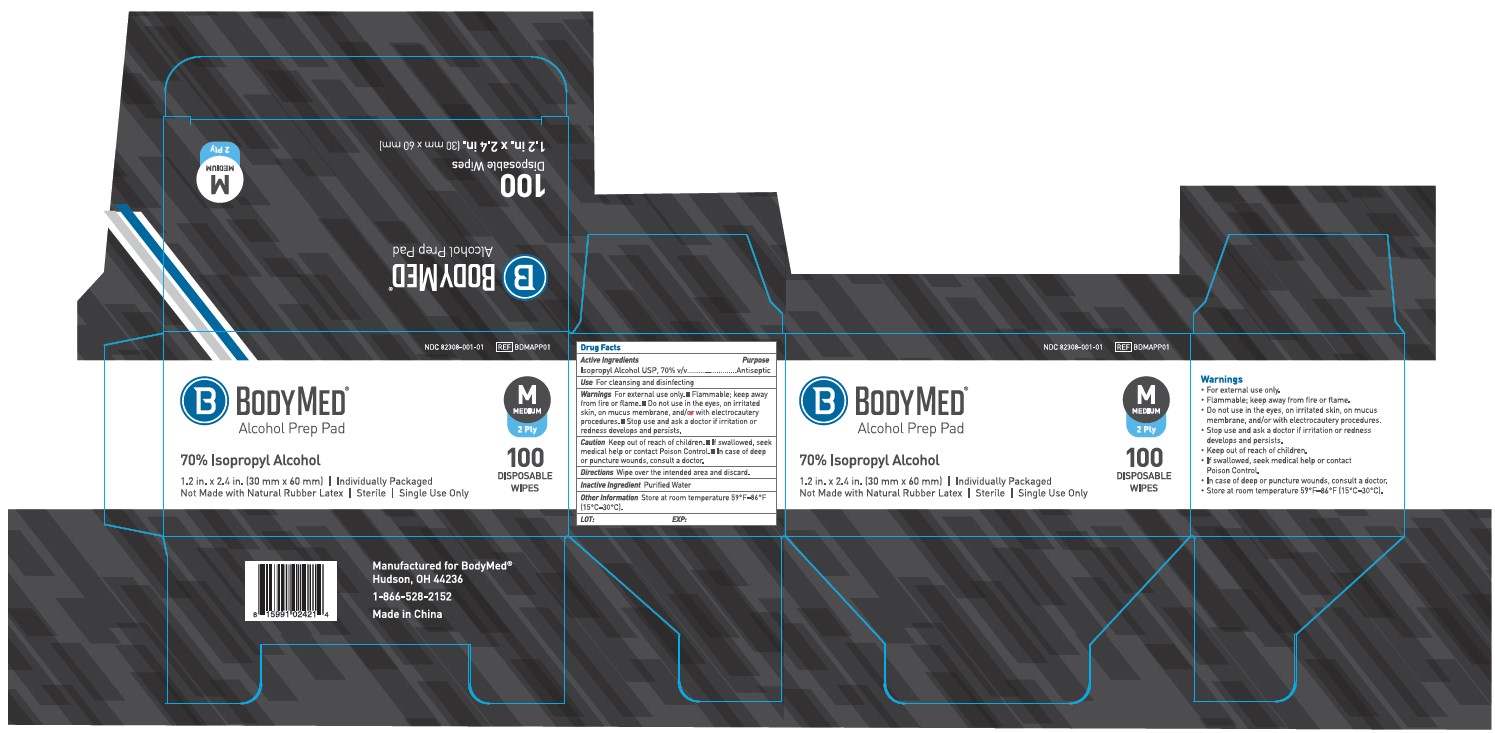 DRUG LABEL: BodyMed Alcohol Prep Pad
NDC: 82308-001 | Form: SWAB
Manufacturer: Boxout, LLC
Category: otc | Type: HUMAN OTC DRUG LABEL
Date: 20251114

ACTIVE INGREDIENTS: ISOPROPYL ALCOHOL 70 mL/100 mL
INACTIVE INGREDIENTS: WATER 30 mL/100 mL

ACTIVE INGREDIENTS

Isopropyl Alcohol USP, 70% v/v

PURPOSE

Antiseptic

USES

For cleasing and disinfecting.

WARNINGS

For external use.only. Flammable; keep away from filre or flame. Do not use in the eyes, on irritated skin, on mucus membrane, and/or with electrocautery procedures.

DIRECTIONS FOR USE

Wipe over the intended area and discard.

OTHER INFORMATION

Store at room temperature 15-30⁰C (59-86⁰F).

INACTIVE INGREDIENT

Water

Directions

Apply to skin as needed
Discard after single use

Directions for use

Wipe over the intended area and discard.

Keep out of reach of children.

If accidentally swallowed, seek medical assistance or immediately contact a Poison Control Center.